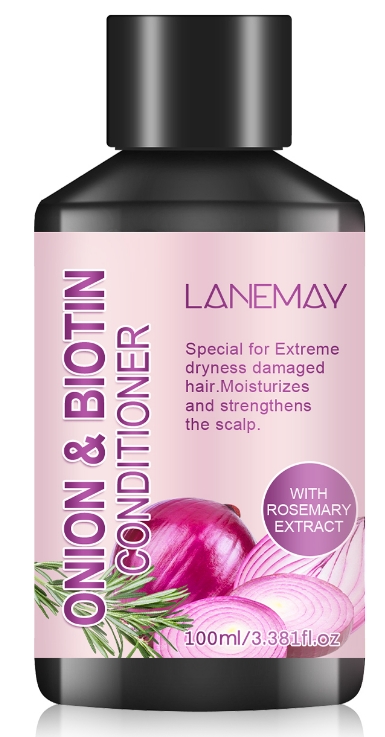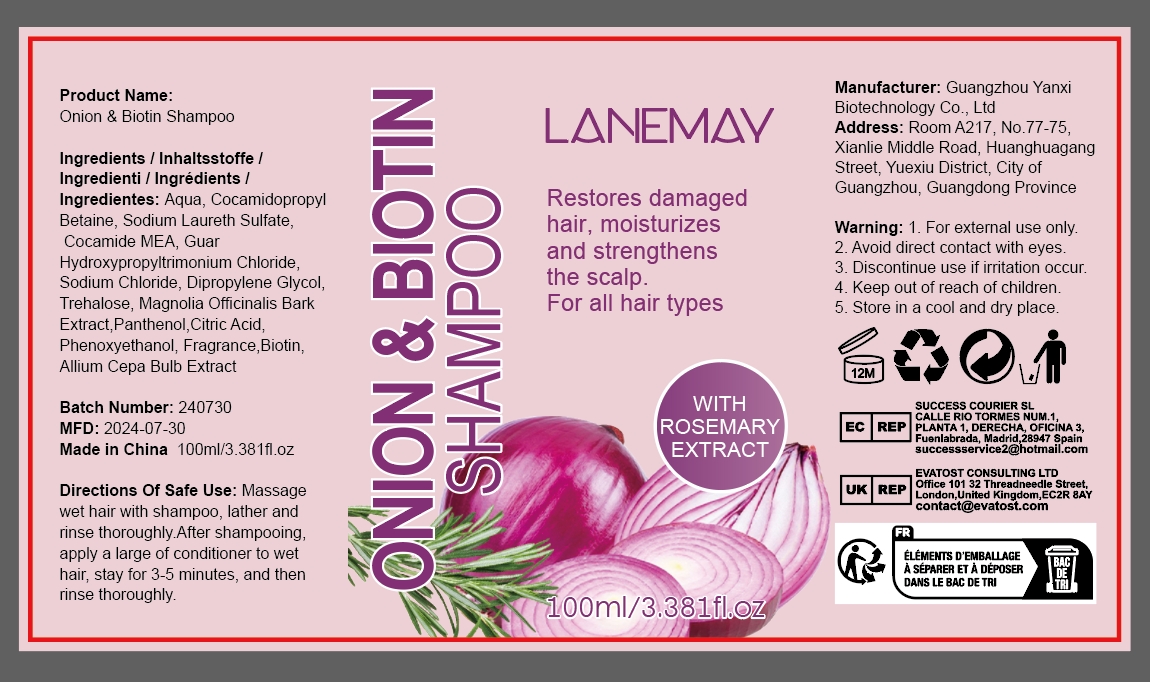 DRUG LABEL: Onion BiotinShampoo
NDC: 84025-175 | Form: SHAMPOO
Manufacturer: Guangzhou Yanxi Biotechnology Co.. Ltd
Category: otc | Type: HUMAN OTC DRUG LABEL
Date: 20240827

ACTIVE INGREDIENTS: COCAMIDOPROPYL BETAINE 5 mg/100 mL; DIPROPYLENE GLYCOL 3 mg/100 mL
INACTIVE INGREDIENTS: WATER

DOSAGE AND ADMINISTRATION

Shampoo for nourishing scalp and smoothing hair

WARNINGS

keep out of children

INACTIVE INGREDIENT

AQUA

INDICATIONS AND USAGE

For daily scalp and hair care

keep out of children

PURPOSE

Effectively maintain scalp health and relieve dry hair